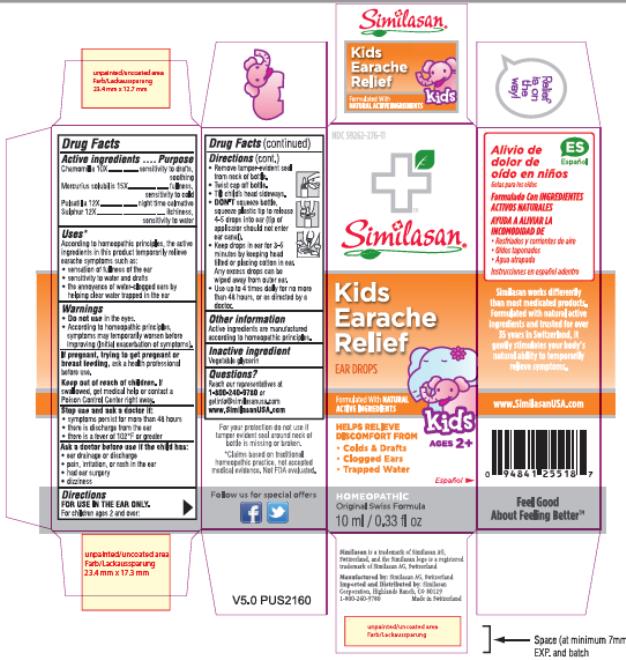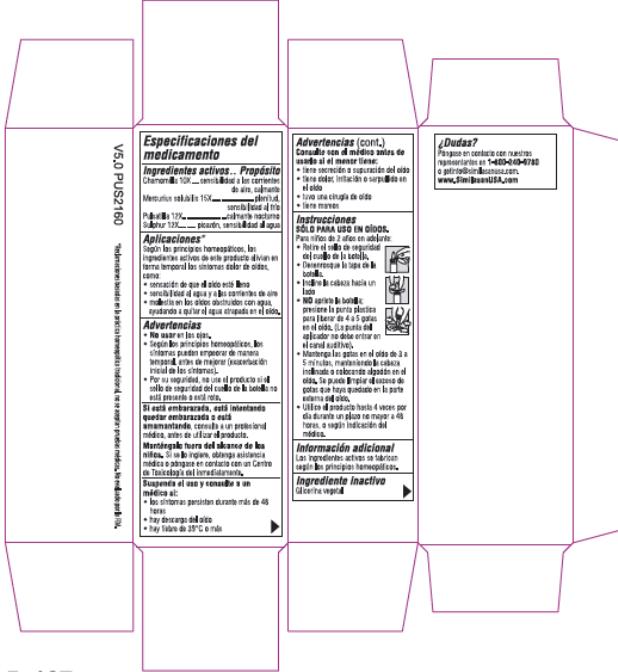 DRUG LABEL: Kids Earache Relief
NDC: 59262-276 | Form: SOLUTION
Manufacturer: Similasan Corporation
Category: homeopathic | Type: HUMAN OTC DRUG LABEL
Date: 20211007

ACTIVE INGREDIENTS: MATRICARIA CHAMOMILLA 10 [hp_X]/10 mL; MERCURIUS SOLUBILIS 15 [hp_X]/10 mL; PULSATILLA PATENS WHOLE 12 [hp_X]/10 mL; SULFUR 12 [hp_X]/10 mL
INACTIVE INGREDIENTS: GLYCERIN

Kids Earache Relief

Drug Facts – Kids Earache Relief

Active ingredients

Chamomilla 10X

Mercurius solubilis 15X

Pulsatilla 12X

Sulphur 12X

Purpose

sensitivity to drafts, soothing

fullness, sensitivity to cold

night time calmative

itchiness, sensitivity to water

Uses*

According to homeopathic principles, the active ingredients in this product temporarily relieve earache symptoms such as:

• sensation of fullness of the ear

• sensitivity to cold, drafts, and water

• the annoyance of water-clogged ears by helping clear water trapped in the ear

Warnings

Do not use

• in the eyes.

• According to homeopathic principles, symptoms may temporarily worsen before improving (Initial exacerbation of symptoms).

If pregnant, trying to get pregnant or breast feeding,

ask a health professional before use.

Keep out of reach of children.

If swallowed, get medical help or contact a Poison Control Center right away.

Stop use and ask a doctor if:

• symptoms persist for more than 48 hours

• there is discharge from the ear

• there is a fever of 102°F or greater

Ask a doctor before use if the child has:

• ear drainage or discharge

• pain, irritation, or rash in the ear

• had ear surgery

• dizziness

Directions

FOR USE IN THE EAR ONLY.

For children ages 2 and over:

• Remove tamper-evident seal from neck of bottle.

• Twist cap off bottle.

• Tilt child’s head sideways.

• DON'T squeeze bottle, squeeze plastic tip to release 4-5 drops into ear (tip of applicator should not enter ear canal).

• Keep drops in ear for 3-5 minutes by keeping head tilted or placing cotton in ear. Any excess drops can be wiped away from outer ear.

• Use up to 4 times daily for no more than 48 hours, or as directed by a doctor.

Other information

Active ingredients are manufactured according to homeopathic principles.

Inactive ingredient

Vegetable glycerin

Questions?

Reach our representatives at 1-800-240-9780 or getinfo@similasanusa.com

www.SimilasanUSA.com

PRINCIPAL DISPLAY PANEL

NDC 59262-276-11
Similasan
Kids
Earache
Relief
EAR DROPS
10 ml / 0.33 fl oz